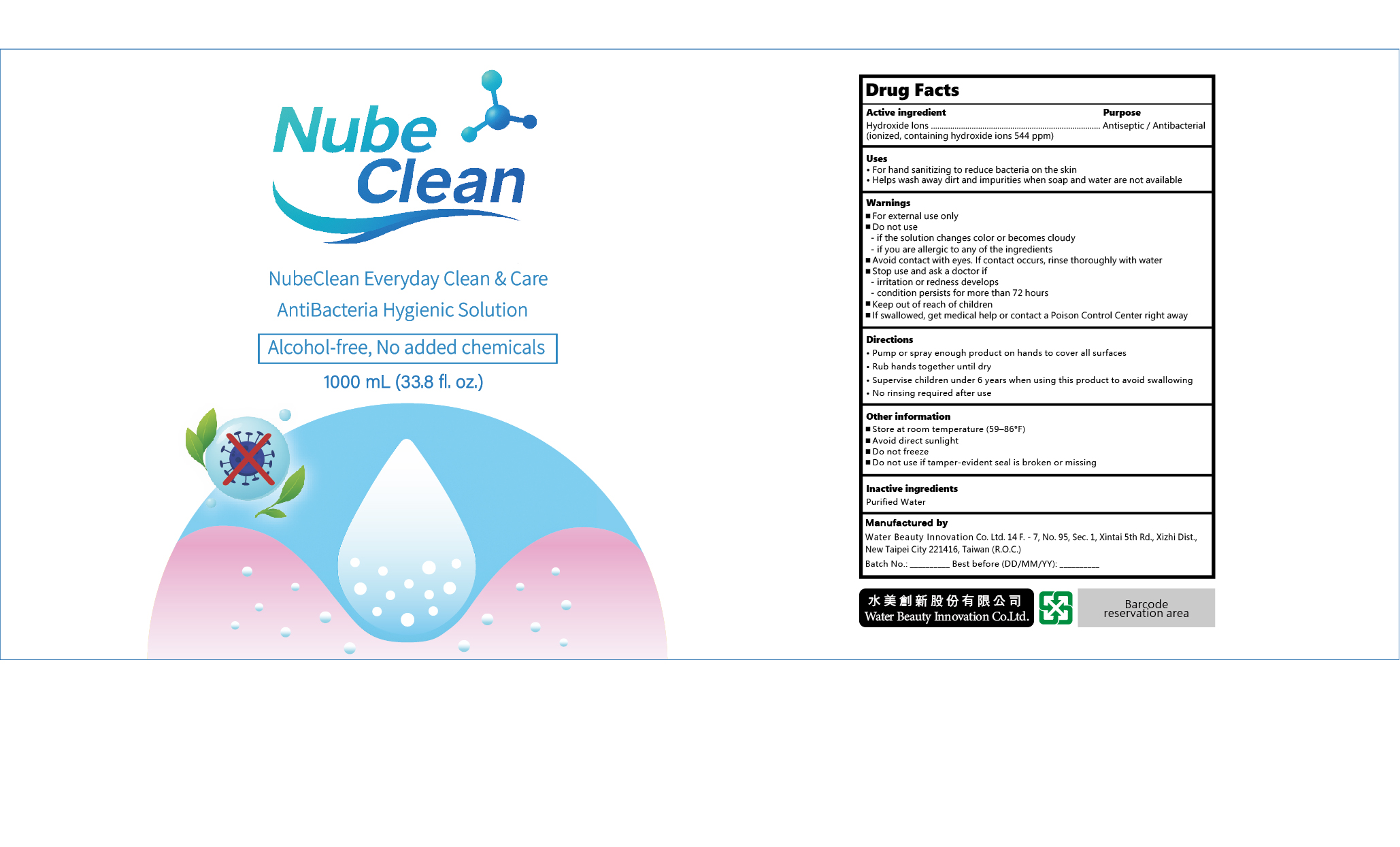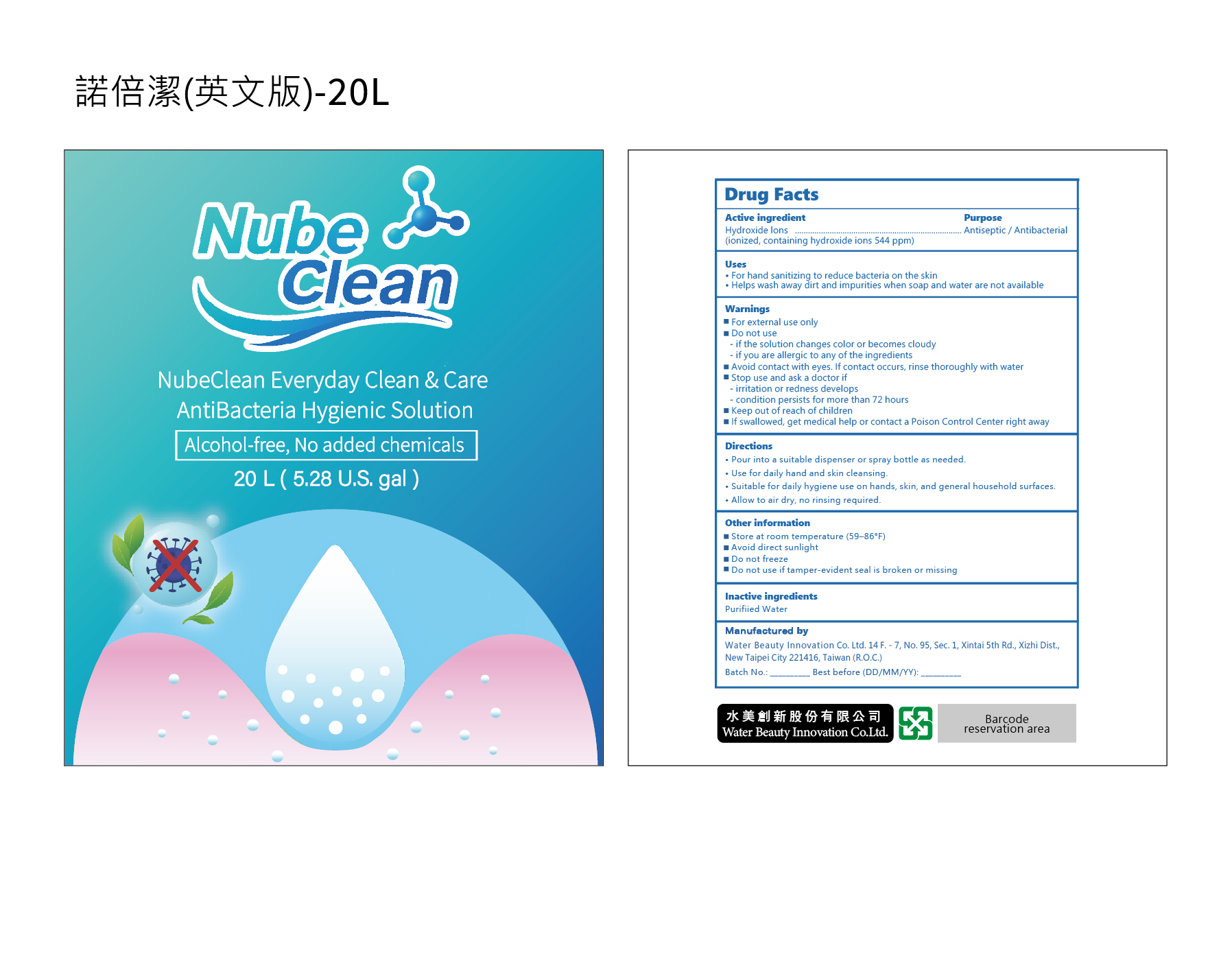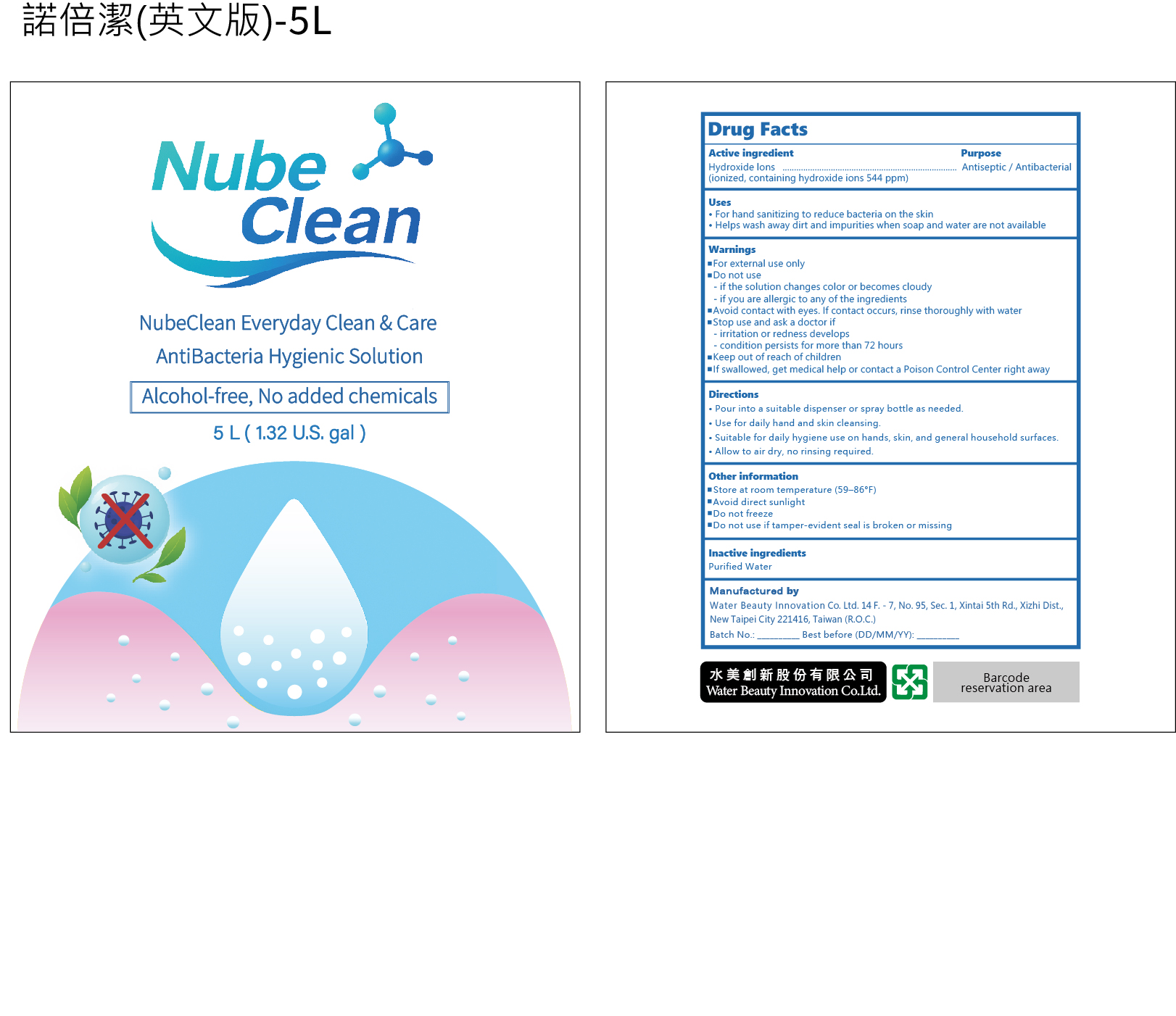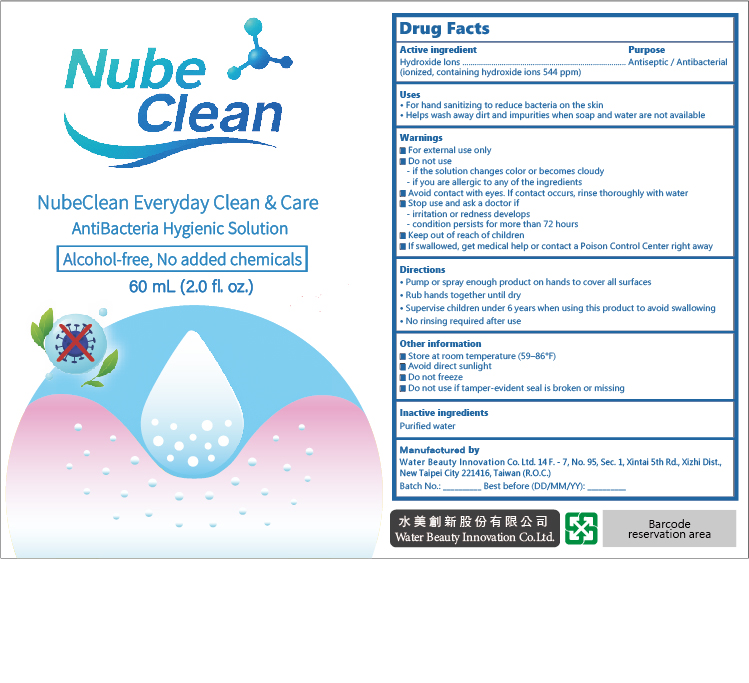 DRUG LABEL: Everyday Clean and Care AntiBacteria Hygienic Solution
NDC: 87406-001 | Form: LIQUID
Manufacturer: Water Beauty Innovation Co. Ltd.
Category: otc | Type: HUMAN OTC DRUG LABEL
Date: 20260212

ACTIVE INGREDIENTS: HYDROXIDE ION 0.2 g/100 mL
INACTIVE INGREDIENTS: WATER

Water Beauty 001-01, 001-02, 001-03, 001-04

ACTIVE INGREDIENT

Hydroxide Ions
(Ionized, containing hydroxide ions 544 ppm)

PURPOSE

Antiseptic / Antibacterial

INDICATIONS AND USAGE

• For hand sanitizing to reduce bacteria on the skin
• Helps wash away dirt and impurities when soap and water are not available

WARNINGS

• For external use only

• Avoid contact with eyes. If contact occurs, rinse thoroughly with water

DO NOT USE

– if the solution changes color or becomes cloudy
– if you are allergic to any of the ingredients

ASK DOCTOR

– irritation or redness develops
– condition persists for more than 72 hours

KEEP OUT OF REACH OF CHILDREN

• If swallowed, get medical help or contact a Poison Control Center right away

DOSAGE AND ADMINISTRATION

• Pour into a suitable dispenser or spray bottle as needed
• Use for daily hand and skin cleansing
• Suitable for daily hygiene use on hands, skin, and general household surfaces
• Allow to air dry, no rinsing required

STORAGE AND HANDLING

• Store at room temperature (59–86°F)
• Avoid direct sunlight
• Do not freeze
• Do not use if tamper-evident seal is broken or missing

INACTIVE INGREDIENT

Purified Water